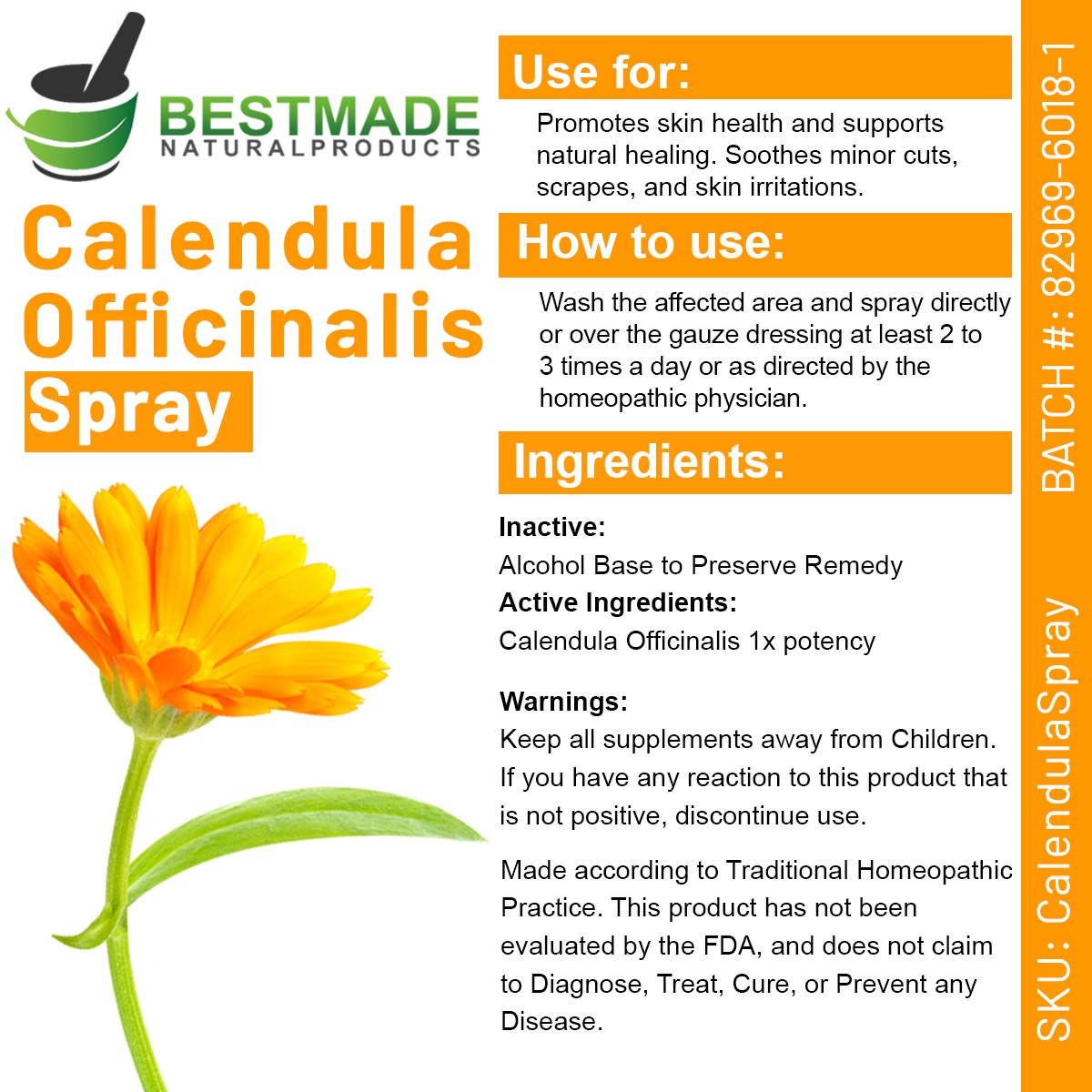 DRUG LABEL: Calendula Officinalis
NDC: 82969-6018 | Form: SPRAY
Manufacturer: Bestmade Natural Products
Category: homeopathic | Type: HUMAN OTC DRUG LABEL
Date: 20250102

ACTIVE INGREDIENTS: CALENDULA OFFICINALIS WHOLE 1 [hp_X]/30 mL
INACTIVE INGREDIENTS: ALCOHOL 30 mL/30 mL

Calendula Officinalis Tincture

DOSAGE AND ADMINISTRATION

How to use:
Wash the affected area and spray directly or over the gauze dressing at least 2 to 3 times a day or as directed by the homeopathic physician.

INDICATIONS AND USAGE

Use for:
Promotes skin health and supports natural healing. Soothes minor cuts, scrapes, and skin irritations.

PURPOSE

Use for:
Promotes skin health and supports natural healing. Soothes minor cuts, scrapes, and skin irritations.

INACTIVE INGREDIENT

Ingredients:
Inactive: Alcohol Base to Preserve Remedy

Active Ingredients: Calendula Officinalis 1x potency

Warnings:
Keep all supplements away from Children.
If you have any reaction to this product that is not positive, discontinue use.

Warnings:
Keep all supplements away from Children.
If you have any reaction to this product that is not positive, discontinue use.
Made according to Traditional Homeopathic Practice.
This product has not been evaluated by the FDA, and does not claim to Diagnose, Treat, Cure, or Prevent any Disease.

entire package label